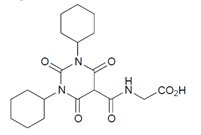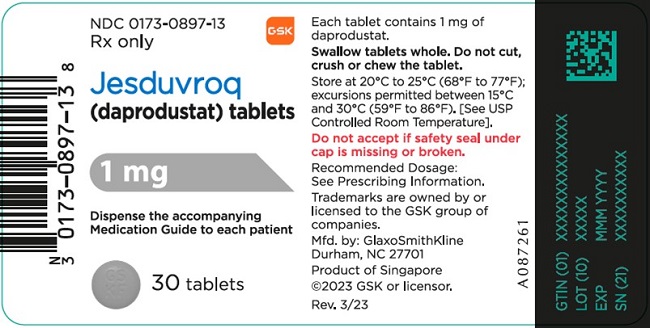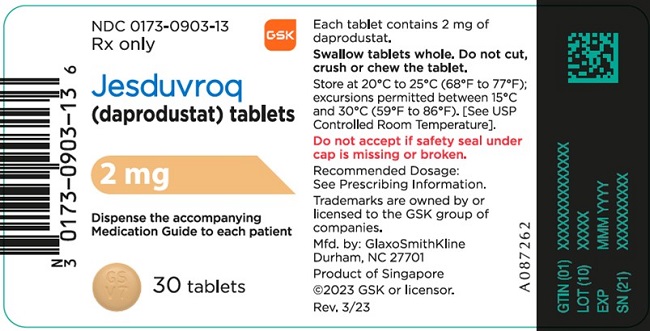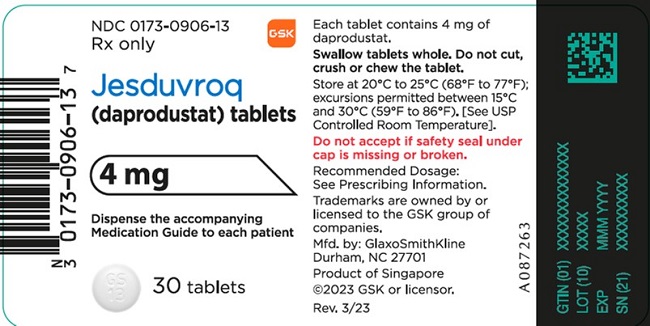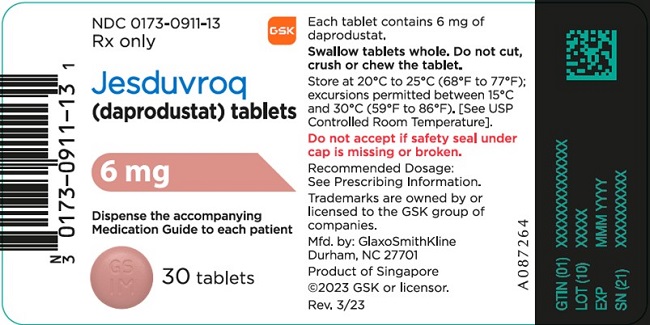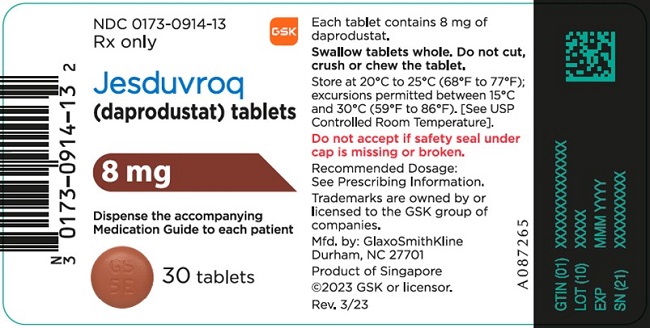 DRUG LABEL: Jesduvroq
NDC: 0173-0897 | Form: TABLET, FILM COATED
Manufacturer: GlaxoSmithKline LLC
Category: prescription | Type: HUMAN PRESCRIPTION DRUG LABEL
Date: 20230830

ACTIVE INGREDIENTS: DAPRODUSTAT 1 mg/1 1
INACTIVE INGREDIENTS: SILICON DIOXIDE; CROSCARMELLOSE SODIUM; HYPROMELLOSE, UNSPECIFIED; MAGNESIUM STEARATE; MANNITOL; MICROCRYSTALLINE CELLULOSE; FERROSOFERRIC OXIDE; FERRIC OXIDE RED; FERRIC OXIDE YELLOW; POLYETHYLENE GLYCOL, UNSPECIFIED; TITANIUM DIOXIDE

HIGHLIGHTS OF PRESCRIBING INFORMATION

These highlights do not include all the information needed to use JESDUVROQ safely and effectively. See full prescribing information for JESDUVROQ.
JESDUVROQ (daprodustat) tablets, for oral use
Initial U.S. Approval: 2023

WARNING: INCREASED RISK OF DEATH, MYOCARDIAL INFARCTION, STROKE, VENOUS THROMBOEMBOLISM, and THROMBOSIS OF VASCULAR ACCESS

See full prescribing information for complete boxed warning.

- JESDUVROQ increases the risk of thrombotic vascular events, including major adverse cardiovascular events (MACE). (5.1)
- Targeting a hemoglobin level greater than 11 g/dL is expected to further increase the risk of death and arterial venous thrombotic events, as occurs with erythropoietin stimulating agents (ESAs), which also increase erythropoietin levels. (5.1)
- No trial has identified a hemoglobin target level, dose of JESDUVROQ, or dosing strategy that does not increase these risks. (2.4)
- Use the lowest dose of JESDUVROQ sufficient to reduce the need for red blood cell transfusions. (2.4)

1 INDICATIONS AND USAGE

JESDUVROQ is a hypoxia-inducible factor prolyl hydroxylase (HIF PH) inhibitor indicated for the treatment of anemia due to chronic kidney disease in adults who have been receiving dialysis for at least four months. (1)

Limitations of Use

Not shown to improve quality of life, fatigue, or patient well-being.

Not indicated for use:

- As a substitute for transfusion in patients requiring immediate correction of anemia.
- In patients not on dialysis.

2 DOSAGE AND ADMINISTRATION

- Administer orally once daily, with or without food. (2.2, 2.3)
- See Full Prescribing Information for starting dosage based on hemoglobin level, liver function and concomitant medications, and for dose titration and monitoring recommendations. (2.3, 2.4, 2.5, 2.6)

3 DOSAGE FORMS AND STRENGTHS

Tablets: 1 mg, 2 mg, 4 mg, 6 mg, and 8 mg. (3)

4 CONTRAINDICATIONS

- Strong cytochrome P450 2C8 (CYP2C8) inhibitors such as gemfibrozil. (4)
- Uncontrolled hypertension. (4)

5 WARNINGS AND PRECAUTIONS

- Risk of Hospitalization for Heart Failure: Increased in patients with a history of heart failure. (5.2)
- Hypertension: Worsening hypertension, including hypertensive crisis may occur. Monitor blood pressure. Adjust anti-hypertensive therapy as needed. (5.3)
- Gastrointestinal Erosion: Gastric or esophageal erosions and gastrointestinal bleeding have been reported. (5.4)
- Not indicated for treatment of anemia of CKD in patients who are not dialysis-dependent (5.5)
- Malignancy: May have unfavorable effects on cancer growth. Not recommended if active malignancy. (5.6)

6 ADVERSE REACTIONS

Most common adverse reactions (incidence ≥10%) are hypertension, thrombotic vascular events, and abdominal pain. (6.1)

To report SUSPECTED ADVERSE REACTIONS, contact GlaxoSmithKline at 1-888-825-5249 or FDA at 1-800-FDA-1088 or www.fda.gov/medwatch.

7 DRUG INTERACTIONS

- Moderate CYP2C8 Inhibitors: Reduce starting dose. (7.1)
- CYP2C8 Inducers: Monitor hemoglobin and adjust the dose of JESDUVROQ as appropriate. (7.2)

8 USE IN SPECIFIC POPULATIONS

- Pregnancy: May cause fetal harm. (8.1)
- Lactation: Breastfeeding not recommended until one week after the final dose. (8.2)
- Hepatic Impairment: Reduce the starting dose in patients with moderate hepatic impairment (Child-Pugh Class B). JESDUVROQ not recommended in severe hepatic impairment (Child-Pugh Class C). (8.6)

FULL PRESCRIBING INFORMATION

WARNING: INCREASED RISK OF DEATH, MYOCARDIAL INFARCTION, STROKE, VENOUS THROMBOEMBOLISM, and THROMBOSIS OF VASCULAR ACCESS

JESDUVROQ increases the risk of thrombotic vascular events, including major adverse cardiovascular events (MACE) [see Warnings and Precautions (5.1)].

Targeting a hemoglobin level greater than 11 g/dL is expected to further increase the risk of death and arterial venous thrombotic events, as occurs with erythropoietin stimulating agents (ESAs), which also increase erythropoietin levels [see Warnings and Precautions (5.1)].

No trial has identified a hemoglobin target level, dose of JESDUVROQ, or dosing strategy that does not increase these risks [see Dosage and Administration (2.4)].

Use the lowest dose of JESDUVROQ sufficient to reduce the need for red blood cell transfusions [see Dosage and Administration (2.4)].

1 INDICATIONS AND USAGE

JESDUVROQ is indicated for the treatment of anemia due to chronic kidney disease (CKD) in adults who have been receiving dialysis for at least four months.

Limitations of Use

JESDUVROQ has not been shown to improve quality of life, fatigue, or patient well-being.

JESDUVROQ is not indicated for use:

- As a substitute for red blood cell transfusions in patients who require immediate correction of anemia.
- For treatment of anemia of chronic kidney disease in patients who are not on dialysis.

2 DOSAGE AND ADMINISTRATION

2.1 Pre-Treatment and On-Treatment Evaluations of Anemia, Iron Stores, and Liver Tests

Evaluation of Anemia and Iron Stores

Correct and exclude other causes of anemia (e.g., vitamin deficiency, metabolic or chronic inflammatory conditions, bleeding) before initiating JESDUVROQ. Evaluate the iron status in all patients before and during treatment with JESDUVROQ. Administer supplemental iron therapy when serum ferritin is less than 100 ng/ml or when serum transferrin saturation is less than 20%. The majority of patients with CKD will require supplemental iron during the course of therapy.

Liver Testing

Assess serum alanine aminotransferase (ALT), aspartate aminotransferase (AST), alkaline phosphatase, and total bilirubin prior to initiation of JESDUVROQ. Repeat the liver tests if the patient develops signs or symptoms that could be consistent with liver disease during treatment with JESDUVROQ.

2.2 Important Dosing Information

Individualize dosing and use the lowest dose of JESDUVROQ sufficient to reduce the need for red blood cell transfusions. Do not target a hemoglobin higher than 11 g/dL.

JESDUVROQ can be taken with or without food, and without regard to concomitant administration of iron or phosphate binders [see Clinical Pharmacology (12.3)].

JESDUVROQ should be swallowed whole. Tablets should not be cut, crushed, or chewed.

JESDUVROQ can be administered without regard to the timing or type of dialysis [see Clinical Pharmacology (12.3)].

If a dose of JESDUVROQ is missed, it should be taken as soon as possible, unless it is the same day as the next dose. In this case, the missed dose should be skipped, and the next dose taken at the usual time. Double-doses should not be taken to make-up for a missed dose.

2.3 Recommended Starting Dose of JESDUVROQ

Adults with Anemia Due to Chronic Kidney Disease Receiving Dialysis for at Least 4 Months

Adults Not Being Treated with an ESA: For adults not being treated with an ESA, the starting dose of JESDUVROQ is based on the hemoglobin level (seeTable 1). Dose modifications are needed for patients receiving concomitant treatment with a moderate CYP2C8 inhibitor or moderate hepatic impairment [see Dosage and Administration (2.5, 2.6), Drug Interactions (7.1), Use in Specific Populations (8.6), Clinical Pharmacology (12.3)].

Table 1: Starting Dose of JESDUVROQ for Adults on Dialysis not Receiving an Erythropoiesis-Stimulating Agent
Pre-Treatment Hemoglobin Level (g/dL) | Starting Dose of JESDUVROQ; (Once Daily Dosing)a
<9 | 4 mg
≥9 to ≤10 | 2 mg
>10 | 1 mg

a See dosing modifications in Section 2.5 if the patient has moderate hepatic impairment and Section 2.6 if the patient is on a moderate CYP2C8 inhibitor.

Adults Being Switched from an ESA: For adults being switched from an ESA to JESDUVROQ, the starting dose of JESDUVROQ is based on the dose regimen of the ESA at the time of substitution (see Table 2). Dose modifications are needed for patients receiving concomitant treatment with a moderate CYP2C8 inhibitor or moderate hepatic impairment [see Dosage and Administration (2.5, 2.6), Drug Interactions (7.1), Use in Specific Populations (8.6), Clinical Pharmacology (12.3)].

Table 2: Starting Dose of JESDUVROQ for Adults on Dialysis Switching from an Erythropoiesis-Stimulating Agent
Current Dose of ESA |  |  | Dose of JESDUVROQa
Epoetin Alfab; Intravenous; (units/week) | Darbepoetin Alfa; Subcutaneous; /Intravenous; (mcg/4 weeks) | Methoxy PEG-Epoetin Beta; Subcutaneous; /Intravenous; (mcg/month) | Once Daily; Dosing
Less than or equal to 2,000 | 20 to 30 | 30 to 40 | 4 mg
Greater than 2,000 to less than 10,000 | Greater than; 30 to 150 | Greater than; 40 to 180 | 6 mg
Greater than or equal to 10,000 to less than 20,000 | Greater than; 150 to 300 | Greater than; 180 to 360 | 8 mg
Greater than or equal to 20,000 | Greater than 300 | Greater than 360 | 12 mg

ESA = Erythropoiesis stimulating agent.

a See dosing modifications in Section 2.5 if the patient has moderate hepatic impairment and Section 2.6 if the patient is on a moderate CYP2C8 inhibitor.
b For patients on subcutaneous epoetin alfa, convert the epoetin alfa subcutaneous dose to intravenous dose equivalent by multiplying the subcutaneous dose received per week by 1.42 to obtain the weekly intravenous dose.

2.4 Monitoring Response to Therapy and Dose Adjustment

Following initiation of therapy and after each dose adjustment, monitor hemoglobin every 2 weeks for the first month and then every 4 weeks thereafter.

When adjusting doses of JESDUVROQ, consider hemoglobin rate of rise, rate of decline and hemoglobin variability. Do not increase the dose of JESDUVROQ more frequently than once every 4 weeks.

- If the dose of JESDUVROQ needs to be adjusted, increase or decrease by one dose level at a time (see Table 3).
- Decrease the dose of JESDUVROQ if hemoglobin increases rapidly (e.g., greater than 1 g/dL over 2 weeks or greater than 2 g/dL over 4 weeks) or if the hemoglobin exceeds 11 g/dL.
- If hemoglobin exceeds 12 g/dL, interrupt treatment with JESDUVROQ. When the hemoglobin is within the target range, treatment may be restarted at one dose level lower (see Table 3).
- Treatment with JESDUVROQ should not be continued beyond 24 weeks of therapy if a clinically meaningful increase in hemoglobin level is not achieved. Alternative explanations for an inadequate response should be sought and treated before re-starting therapy.

Table 3: Dose Levels of JESDUVROQ
Daily dose of JESDUVROQ | 1 mg | 2 mg | 4 mg | 6 mg | 8 mg | 12 mg | 16 mg | 24 mga

a 24 mg is the maximum recommended once daily dose.

2.5 Dosage Modification for Hepatic Impairment

Reduce the starting dose of JESDUVROQ by half (see Table 1 and Table 2) in patients with moderate hepatic impairment (Child-Pugh Class B) except in patients whose starting dose is already 1 mg.

Use of JESDUVROQ in patients with severe hepatic impairment (Child-Pugh Class C) is not recommended [see Use in Specific Populations (8.6), Clinical Pharmacology (12.3)].

2.6 Dosage Modification for Concomitant Treatment with Moderate CYP2C8 Inhibitors

Reduce the starting dose of JESDUVROQ by half (see Table 1 and Table 2) in patients who are on clopidogrel or a moderate CYP2C8 inhibitor except in patients whose starting dose is already 1 mg [see Drug Interactions (7.1), Clinical Pharmacology (12.3)].

Monitor hemoglobin and adjust the dose of JESDUVROQ when initiating or stopping therapy with clopidogrel or a moderate CYP2C8 inhibitor during treatment with JESDUVROQ.

3 DOSAGE FORMS AND STRENGTHS

Tablets:

- 1 mg, gray, biconvex, round film-coated tablets debossed with “GS KF” on one face.
- 2 mg, yellow, biconvex, round film-coated tablets debossed with “GS V7” on one face.
- 4 mg, white, biconvex, round film-coated tablets debossed with “GS 13” on one face.
- 6 mg, pink, biconvex, round film-coated tablets debossed with “GS IM” on one face.
- 8 mg, orange, biconvex, round film-coated tablets debossed with “GS 5E” on one face.

4 CONTRAINDICATIONS

JESDUVROQ is contraindicated in patients:

- Receiving a strong CYP2C8 inhibitor such as gemfibrozil [see Drug Interactions (7.1), Clinical Pharmacology (12.3)].
- With uncontrolled hypertension [see Warnings and Precautions (5.3)].

5 WARNINGS AND PRECAUTIONS

5.1 Increased Risk of Death, Myocardial Infarction, Stroke, Venous Thromboembolism, and Thrombosis of Vascular Access

JESDUVROQ increases the risk of arterial and venous thrombotic events, that may be fatal, including myocardial infarction, stroke, venous thromboembolism and vascular access thrombosis [see Boxed Warning, Adverse Reactions (6.1)]. Patients with cardiovascular or cerebrovascular disease are at increased risk of these events. Avoid use in patients with a history of myocardial infarction, cerebrovascular event, or acute coronary syndrome within the 3 months prior to starting JESDUVROQ.

A rate of hemoglobin rise of greater than 1 g/dL over 2 weeks may contribute to these risks. Targeting a hemoglobin level of greater than 11 g/dL is expected to further increase the risk of death and arterial and venous thrombotic events, as occurs with ESAs, which also increase erythropoietin levels.

No trial has identified a hemoglobin target level, dose of JESDUVROQ, or dosing strategy that does not increase these risks. Use the lowest dose of JESDUVROQ sufficient to reduce the need for red blood transfusions. Adherence to dosing and hemoglobin monitoring recommendations is important to avoid excessive erythropoiesis [see Dosage and Administration (2.4)].

Advise patients to seek immediate medical attention if they develop signs or symptoms of myocardial infarction, stroke, venous thromboembolism, or thrombosis of vascular access. Evaluate and manage promptly if these occur.

5.2 Risk of Hospitalization for Heart Failure

In the ASCEND-D trial, hospitalization for heart failure was observed in 7.5% (3.3 per 100 Person Years [PY]) of patients on dialysis receiving JESDUVROQ and 6.8% (3.0 per 100 PY) of patients receiving recombinant human erythropoietin (rhEPO). Patients with a pre-existing history of heart failure were at increased risk of hospitalization for heart failure with JESDUVROQ (14.5%; 6.8 per 100 PY) compared to rhEPO (11.3%; 5.1 per 100 PY).

Consider the patient’s history of heart failure when deciding whether to prescribe JESDUVROQ. Advise patients of the symptoms and signs of heart failure and to immediately report any worsening to their healthcare provider.

5.3 Hypertension

JESDUVROQ is contraindicated in patients with uncontrolled hypertension. In the ASCEND-D trial, worsening of hypertension occurred in 24% (12 per 100 PY) of patients receiving JESDUVROQ and 24% (12 per 100 PY) of patients receiving rhEPO [see Adverse Reactions (6.1)]. Serious worsening of hypertension occurred in 3.1% of patients receiving JESDUVROQ and 3.1% of patients receiving rhEPO. Cases of hypertensive crisis including hypertensive encephalopathy and seizures have also been reported in patients receiving JESDUVROQ. Periodically monitor blood pressure and adjust or initiate anti-hypertensive therapy as needed.

5.4 Gastrointestinal Erosion

In the ASCEND-D trial, gastric or esophageal erosions occurred in 5.7% (2.5 per 100 PY) of patients receiving JESDUVROQ and 6.6% (2.9 per 100 PY) of rhEPO-treated patients. Serious erosions, including gastrointestinal bleeding and the need for red blood cell transfusions, were reported in 3.6% and 3.1% of those receiving JESDUVROQ and rhEPO, respectively. Consider this risk particularly in patients at increased risk for gastrointestinal erosions, such as those with a history of gastrointestinal erosion, peptic ulcer disease, use of concomitant medications that increase the risk of gastrointestinal erosion, and current tobacco smokers and alcohol drinkers.

Advise patients of the symptoms and signs of gastric and esophageal erosions and of gastrointestinal bleeding and to seek prompt medical care if these occur.

5.5 Serious Adverse Events in Patients with Anemia Due to Chronic Kidney Disease and Not on Dialysis

The safety of JESDUVROQ has not been established for the treatment of anemia due to CKD in adults not on dialysis and its use is not recommended in this setting [see Indications and Usage (1)].

In a large cardiovascular outcomes trial in adults with anemia of CKD who were not on dialysis (ASCEND-ND), an increased risk of cardiovascular mortality, stroke, thromboembolism, serious acute kidney injury, hospitalization for heart failure, and serious gastrointestinal erosions was observed in patients treated with JESDUVROQ compared to rhEPO.

5.6 Malignancy

Because increased hypoxia inducible factor (HIF)-1 levels may be associated with unfavorable effects on cancer growth, JESDUVROQ has not been studied and is not recommended in patients with active malignancies. Malignancies were observed in 4.4% (1.9 per 100 PY) of patients treated with JESDUVROQ and 5.2% (2.3 per 100 PY) of patients treated with rhEPO. No evidence of increased carcinogenicity was observed in animal studies [see Nonclinical Toxicology (13.1)].

6 ADVERSE REACTIONS

The following clinically significant adverse reactions are described elsewhere in the labeling:

- Increased Risk of Death, Myocardial Infarction, Stroke, Venous Thromboembolism, and Thrombosis of Vascular Access [see Boxed Warning, Warnings and Precautions (5.1)].
- Risk of Hospitalization for Heart Failure [see Warnings and Precautions (5.2)].
- Hypertension [see Warnings and Precautions (5.3)].
- Gastrointestinal Erosion [see Warnings and Precautions (5.4)].

6.1 Clinical Trials Experience

Because clinical trials are conducted under widely varying conditions, adverse reaction rates observed in the clinical trials of a drug cannot be directly compared with rates in the clinical trials of another drug and may not reflect the rates observed in practice.

The safety of JESDUVROQ was evaluated in adults with dialysis-dependent chronic kidney disease with anemia in the ASCEND-D trial based on an on-study analysis (on and off treatment) [see Clinical Studies (14.1)]. Patients were randomized to JESDUVROQ or rhEPO (epoetin alfa for patients on hemodialysis; darbepoetin alfa for patients on peritoneal dialysis). Of the 2,964 patients randomized in the trial, 1,487 were randomized to JESDUVROQ, 1,316 (88.5%) of whom were on hemodialysis and 171 (11.5%) of whom were on peritoneal dialysis.

The median extent of exposure to JESDUVROQ and rhEPO was similar. In the JESDUVROQ treatment arm, 65% of the participants were exposed to at least 18 months of JESDUVROQ and 29% of participants received JESDUVROQ for at least 2.5 years.

JESDUVROQ was non-inferior to rhEPO on the time to first occurrence of major adverse cardiovascular events (MACE) in adults with anemia due to CKD who were on dialysis [see Clinical Studies (14.1)].

Permanent treatment discontinuation due to an adverse reaction was reported in 19% of patients treated with JESDUVROQ and 18% of patients treated with rhEPO. No specific adverse reaction resulted in permanent treatment discontinuation in >1% of patients treated with JESDUVROQ.

The most common adverse reactions (≥10% of JESDUVROQ-treated patients) were hypertension, thrombotic vascular events, and abdominal pain.

Table 4 lists the most common adverse reactions (reported in ≥5% of patients treated with JESDUVROQ).

Table 4: Adverse Reactions Reported in ≥5% of Patients Treated with JESDUVROQ in the ASCEND-D Trial
Adverse Reaction | JESDUVROQ; (n = 1,482); % | rhEPO; (n = 1,474); %
Hypertension | 24 | 24
Abdominal paina | 11 | 8
Dizziness | 7 | 6
Hypersensitivityb | 7 | 7

rhEPO = Recombinant human erythropoietin.

a Includes unspecified abdominal pain, upper abdominal pain, abdominal discomfort.

b Includes rash, urticaria and dermatitis.

Thrombotic Vascular Events

Adjudicated thrombotic vascular events (fatal and non-fatal) were observed in 9.8 per 100 PY of patients receiving JESDUVROQ and in 11.7 per 100 PY of patients receiving rhEPO (see Table 5).

Table 5: Adjudicated Thrombotic Vascular Events (Fatal and Non-Fatal) in the ASCENDD Triala
Event | JESDUVROQ; (n = 1,482) | rhEPO; (n = 1,474)
Event | Rate per 100 PY | Rate per 100 PY
Vascular access thrombosis | 5.0 | 6.3
Myocardial infarction | 3.4 | 4.1
Stroke | 1.2 | 1.5
Deep vein thrombosis | 0.7 | 0.6
Pulmonary embolism | 0.3 | 0.4

PY = Person Years; rhEPO = Recombinant human erythropoietin.

a These data are not an adequate basis for comparison of rates between the study drug and the active control.

7 DRUG INTERACTIONS

7.1 CYP2C8 Inhibitors

Concomitant administration of strong CYP2C8 inhibitors (e.g., gemfibrozil) with JESDUVROQ is contraindicated due to a marked increase in daprodustat exposure [see Contraindications (4), Clinical Pharmacology (12.3)]. Concomitant administration of moderate CYP2C8 inhibitors (e.g., clopidogrel) increases daprodustat exposure [see Clinical Pharmacology (12.3)]. Reduce the starting dose of JESDUVROQ by half when initiating treatment in patients on clopidogrel or a moderate CYP2C8 inhibitor except in patients whose starting dose is already 1 mg. Monitor hemoglobin and adjust the dose of JESDUVROQ when initiating or stopping therapy with clopidogrel or a moderate CYP2C8 inhibitor during treatment with JESDUVROQ [see Dosage and Administration (2.6)].

7.2 CYP2C8 Inducers

CYP2C8 inducers (e.g., rifampin) may decrease daprodustat exposure, which may result in loss of efficacy. Monitor hemoglobin and adjust the dose of JESDUVROQ when initiating or stopping therapy with CYP2C8 inducers during treatment with JESDUVROQ [see Clinical Pharmacology (12.3)].

8 USE IN SPECIFIC POPULATIONS

8.1 Pregnancy

Risk Summary

Available data with JESDUVROQ use in pregnant women are insufficient to establish a drug associated risk of major birth defects, miscarriage, or adverse maternal or fetal outcomes. There are risks to the mother and the fetus associated with CKD (see Clinical Considerations). Daprodustat administered orally to pregnant rats and rabbits during the period of organogenesis was associated with adverse fetal outcomes, including embryonic and fetal loss and reduced fetal weight, at doses that caused maternal toxicity and polycythemia (see Data). Advise pregnant women of the potential risk to the fetus.

The background risk of major birth defects and miscarriage for the indicated population is unknown. All pregnancies have a background risk of birth defect, loss, or other adverse outcomes. In the U.S. general population, the estimated background risk of major birth defects and miscarriage in clinically recognized pregnancies is 2% to 4% and 15% to 20%, respectively.

Clinical Considerations

Disease-Associated Maternal and/or Embryo/Fetal Risk: CKD in pregnancy increases the risk for maternal hypertension, preeclampsia, miscarriage, stillbirth, preterm delivery, low birth weight infants, and polyhydramnios.

Data

Animal Data: Daprodustat was orally administered to pregnant rats at 0.5, 7, or 60 mg/kg/day from gestation day 6 to gestation day 17 during the period of organogenesis. No adverse effects were observed at doses less than or equal to 7 mg/kg/day (3 times the maximum recommended human dose [MRHD] based on body surface area). Daprodustat administration resulted in post-implantation loss, increased embryofetal death, and reduction in skeletal ossification in rats at a dose of 60 mg/kg/day (24 times the MRHD based on body surface area), which was associated with maternal toxicity (reduced body weight gain or weight loss). Maternal toxicity occurred at doses associated with polycythemia.

Daprodustat was orally administered to pregnant rabbits at doses of 4, 30, or 60 mg/kg/day from gestation day 7 until gestation day 19 during the period of organogenesis. No adverse effects were observed at doses less than or equal to 30 mg/kg/day (24 times the MRHD based on body surface area). Daprodustat administration was associated with a low incidence of abortions and fetal skeletal malformations (irregularly shaped anterior fontanelle, manubrium, fused sternal centra, and microphthalmia) at a dose of 60 mg/kg/day (49 times the MRHD based on body surface area) in the presence of maternal toxicity (reduced body weight gain or weight loss) and polycythemia.

In a pre- and postnatal development study, pregnant rats were dosed orally with daprodustat from implantation until weaning (gestation day 6 to lactation day 21) at 0.8, 7, or 40 mg/kg/day concomitantly with 3 major human metabolites of daprodustat. No adverse effects were observed at doses less than or equal to 7 mg/kg/day (3 times the MRHD based on body surface area). Maternal toxicity (in the presence of polycythemia) was noted at 40 mg/kg/day (16 times the MRHD based on body surface area), which was associated with increased pup deaths and decreased pup weights.

8.2 Lactation

Risk Summary

There are no data on the presence of daprodustat in human milk, the effects on the breastfed child, or the effects on milk production. Daprodustat is present in the milk of lactating rats (see Data). When a drug is present in animal milk, it is likely that the drug will be present in human milk. Given the serious adverse reactions seen in adults treated with JESDUVROQ, such as thrombotic vascular events, advise patients not to breastfeed during treatment with JESDUVROQ, and for one week after the final dose.

Data

In a pre- and postnatal development study in rats, when daprodustat was orally administered to maternal rats during the lactation period, the drug was detected in plasma of suckling pups on postnatal day 10. The plasma concentration of daprodustat in pups was 2.3% to 3.7% of daprodustat detected in the plasma of dams when dosed at 40 mg/kg/day.

8.4 Pediatric Use

Safety and effectiveness of JESDUVROQ in pediatric patients have not been established.

8.5 Geriatric Use

Of the total number of subjects treated with JESDUVROQ in the ASCEND-D study (n = 2,964), 480 (32%) subjects were aged 65 years and older, and 159 (11%) were aged 75 years and older. No overall differences in safety or effectiveness were observed between these subjects and younger subjects. No other reported clinical experience has identified differences in responses between the elderly and younger patients.

8.6 Hepatic Impairment

No adjustment of the starting dose is required in patients with mild hepatic impairment (Child-Pugh Class A).

Reduce the starting dose of JESDUVROQ by half in patients with moderate hepatic impairment (Child-Pugh Class B) except in patients whose starting dose is already 1 mg [see Clinical Pharmacology (12.3)].

JESDUVROQ has not been studied in patients with severe hepatic impairment (Child-Pugh Class C). Therefore, JESDUVROQ is not recommended in patients with severe hepatic impairment.

9 DRUG ABUSE AND DEPENDENCE

9.1 Controlled Substance

JESDUVROQ contains daprodustat, which is not a controlled substance.

9.2 Abuse

Drug abuse is intentional non-therapeutic use of a drug, even once, for its rewarding psychological or physiological effects. Abuse of JESDUVROQ may be seen in athletes for the effects on erythropoiesis.

Abuse-Related Adverse Reactions

There are no data on the abuse of JESDUVROQ in humans. Daprodustat and its metabolites neither selectively penetrate the central nervous system, nor produce behavioral effects in animals that are consistent with central nervous system activity.

Misuse of drugs that increase erythropoiesis, such as JESDUVROQ, by healthy persons may lead to polycythemia, which may be associated with life-threatening cardiovascular complications (e.g., stroke, myocardial infarction, and thromboembolism).

10 OVERDOSAGE

Headache and gastrointestinal adverse reactions (e.g., nausea) may be seen with acute overdose with JESDUVROQ. There is no specific antidote. Hemodialysis will not substantially remove daprodustat because it is highly protein bound.

11 DESCRIPTION

JESDUVROQ contains daprodustat, an inhibitor of hypoxia inducible factor (HIF), prolyl 4-hydroxylases (PH)1, PH2 and PH3. The chemical name of daprodustat is N‑[(1,3‑dicyclohexylhexahydro-2,4,6-trioxopyrimidin-5-yl) carbonyl]glycine. The molecular formula of daprodustat is C19H27N3O6, and its molecular mass is 393.43. The structural formula is shown below.

Daprodustat is a white to off-white powder that is poorly soluble in water.

Each JESDUVROQ oral tablet contains 1 mg, 2 mg, 4 mg, 6 mg, or 8 mg of daprodustat. Inactive ingredients include colloidal silicon dioxide, croscarmellose sodium, hypromellose, magnesium stearate, mannitol and microcrystalline cellulose. The tablet film-coating inactive ingredients include hypromellose, iron oxide black (1 mg, 2 mg, and 6 mg tablets), iron oxide red and iron oxide yellow (1 mg, 2 mg, 6 mg, and 8 mg tablets), polyethylene glycol, and titanium dioxide.

12 CLINICAL PHARMACOLOGY

12.1 Mechanism of Action

Daprodustat is a reversible inhibitor of HIF-PH1, PH2 and PH3 (IC50 in the low nM range). This activity results in the stabilization and nuclear accumulation of HIF-1α and HIF-2α transcription factors, leading to increased transcription of the HIF-responsive genes, including erythropoietin.

12.2 Pharmacodynamics

Effects on Erythropoiesis

Daprodustat increases endogenous erythropoietin in a dose-dependent manner within 6 to 8 hours after administration. With repeat doses, peak increases in reticulocyte counts occur between 7 and 15 days, with subsequent increases in red blood cell production. New hemoglobin steady-state levels are reached several weeks (approximately 4 weeks in ESA-users and approximately 16-20 weeks in ESA-non-users) after initial administration.

Effects on Iron Metabolism and Utilization

Daprodustat increased serum transferrin and total iron binding capacity (TIBC) and decreased serum ferritin, transferrin saturation, and hepcidin when administered for 52 weeks in adults on dialysis with anemia due to CKD.

Cardiac Electrophysiology

At a dose 10 times the maximum recommended dose, daprodustat does not prolong the QTc interval to any clinically relevant extent.

12.3 Pharmacokinetics

Daprodustat exposure generally increases in a dose-proportional manner over the range of approved doses. Steady-state concentrations are achieved within 24-hours of dosing.

Absorption

Following oral administration, daprodustat is readily absorbed with median time to peak concentration (Tmax) in healthy subjects ranging from 1 hour to 4 hours. The absolute bioavailability of daprodustat is 65%. Administration of JESDUVROQ with a high fat/high calorie meal did not significantly alter daprodustat exposure compared to administration in the fasted state.

Distribution

Daprodustat has an approximately equal distribution between plasma and blood cells (blood:plasma ratio of 1.23). Following intravenous dosing, the volume of distribution at steady-state in healthy subjects is 14.3 L. In vitro, plasma protein binding of daprodustat is >99%.

Elimination

The terminal elimination half-life of daprodustat is approximately 1 hour to 4 hours.

Metabolism: In vitro, daprodustat is primarily metabolized by CYP2C8 (95% contribution), with a minor contribution by CYP3A4 (5%).

Following oral or intravenous administration of radiolabeled daprodustat to healthy adults, approximately 40% of the total circulating radioactivity in plasma was daprodustat, and the remaining 60% was metabolites.

In patients treated with JESDUVROQ, the parent drug is the principal circulating component in plasma. Three metabolites, each accounting for more than 10% of circulating drug-related material, have been identified; in vitro and non-clinical data suggest that each may contribute to the pharmacologic response in vivo; however, the extent of this contribution is unknown.

Excretion: Mean clearance from plasma was 18.9 L/h, which correlates to blood clearance of 15 L/h and equates to a hepatic extraction of approximately 18%.

Within seven days of an oral dose of radiolabeled daprodustat, 74% of the radioactivity was recovered in the feces, and 21% in the urine. Approximately 99.5% of the dose was excreted as oxidative metabolites, with the rest accounted for by daprodustat.

Specific Populations

Elderly: Population pharmacokinetic analyses in adults with CKD (22 years to 93 years) showed that age did not influence the pharmacokinetics of daprodustat.

Renal Impairment: The steady-state exposure of daprodustat is similar in patients with normal renal function and those with varying degrees of renal impairment; daprodustat exposure is not significantly impacted by hemodialysis or peritoneal dialysis. The systemic exposure of daprodustat metabolites was higher in patients with Stage 3 to 5 CKD compared to those with normal renal function. Exposures of metabolites were higher on non-dialysis days compared to dialysis days.

Hepatic Impairment: Following administration of a single JESDUVROQ 6 mg dose, mean daprodustat Cmax and AUC increased by 2-fold and unbound exposure increased by 2.3-fold in subjects with moderate hepatic impairment (Child‑Pugh Class B) compared to subjects with normal hepatic and renal function. For those with mild hepatic impairment (Child‑Pugh Class A), mean daprodustat Cmax was similar while AUC increased by 1.5-fold and unbound Cmax and AUC increased by 1.6 and 2.2-fold, respectively, compared to subjects with normal hepatic and renal function. The effect of severe hepatic impairment (Child‑Pugh Class C) on the pharmacokinetics of daprodustat is unknown as there have been no studies of JESDUVROQ in patients with severe hepatic impairment.

Drug Interaction Studies

Clinical Studies: Effect of CYP2C8 Inhibitors on the Pharmacokinetics of Daprodustat: The concomitant administration of gemfibrozil 600 mg twice a day for 5 days (strong CYP2C8 inhibitor) with a single 100 mg dose of JESDUVROQ on Day 4 of gemfibrozil administration resulted in an 18.6‑fold increase in AUC(0-∞) and a 3.9-fold increase in Cmax of daprodustat [see Contraindications (4)].

The concomitant administration of trimethoprim 200 mg twice a day for 5 days (CYP2C8 weak inhibitor) and 25 mg single dose of JESDUVROQ on Day 4 of trimethoprim administration resulted in a 1.5-fold increase in AUC(0-∞) and a 1.3‑fold increase in Cmax of daprodustat.

Daprodustat AUC and Cmax are expected to increase at least 4-fold and 3-fold, respectively, following concomitant administration of daprodustat with clopidogrel 75 mg once daily (moderate CYP2C8 inhibitor).

Following 4 weeks of JESDUVROQ dosing, hemoglobin changes from baseline were similar in subjects with and without concomitant use of clopidogrel.

Effect of Daprodustat on the Pharmacokinetics of Other Drugs: Clinical drug interaction studies showed that daprodustat inhibition of CYP2C8 and OATP1B1/OATP1B3 demonstrated no clinically significant effect on pioglitazone (CYP2C8 substrate) or rosuvastatin (OATP1B1/OATP1B3 substrate) Cmax or AUC.

In vitro studies: Some oxidative metabolites of daprodustat are substrates of Organic Anion Transporter (OAT)1 or OAT3; however, the clinical significance of this is unknown. Daprodustat is a substrate of Breast Cancer Resistance Protein (BCRP); however, the risk of significant drug interactions between daprodustat and BCRP inhibitors is considered low given the absorption and metabolism profile of daprodustat.

Daprodustat is not an inducer of CYP1A2, CYP2B6 and CYP3A4. Daprodustat is not an inhibitor of P-glycoprotein (P-gp) and BCRP.

Daprodustat is not a substrate of CYP1A2, CYP2B6, CYP2C9, CYP2C19, CYP2D6 and P-gp. The major metabolites are not substrates of OATP1B1, OATP1B3, OATP2B1, Organic Cation Transporter (OCT)1, OCT2, Multidrug and Toxin Extrusion (MATE)1 and MATE2-K. Daprodustat and its major metabolites are not inhibitors of CYP1A2, CYP2A6, CYP2B6, CYP2C9, CYP2C19, CYP2D6, CYP3A4, OATP1B1, OATP1B3, OATP2B1, OCT1, OAT1, OAT3, OCT2, MATE1 and MATE2-K.

13 NONCLINICAL TOXICOLOGY

13.1 Carcinogenesis, Mutagenesis, Impairment of Fertility

Daprodustat was not carcinogenic in two-year carcinogenicity studies when administered orally at doses of 0.02, 0.1, 0.8, or 4 mg/kg/day (males) / 7 mg/kg/day (females) in rats (up to 3 times the MRHD based on body surface area) and 0.2, 0.8, or 3 mg/kg/day (including subcutaneous injection of major human metabolites of daprodustat) in mice (approximating the MRHD based on body surface area).

Daprodustat was negative for mutagenic or clastogenic potential in the in vitro bacterial reverse mutation assay, the in vitro human lymphocyte chromosomal aberration assay, and the in vivo rat bone marrow micronucleus assay.

In a fertility and early embryonic development study in rats, daprodustat was administered orally at doses of 2, 7, or 100 mg/kg/day in females, resulting in maternal toxicity of reduced body weight gain and decreased mean uterine weight (in the presence of polycythemia), associated with decreased number of corpora lutea, implantations, and live fetuses, and increased post-implantation loss at the dose of 100 mg/kg/day (41 times the MRHD based on body surface area).

14 CLINICAL STUDIES

14.1 Anemia Due to Chronic Kidney Disease in Adults on Dialysis

The efficacy and safety of JESDUVROQ were evaluated in 2,964 adults with anemia due to CKD on dialysis and receiving an ESA at the time of study entry in a randomized, sponsor-blind, active-controlled, global, multicenter, event-driven clinical trial (ASCEND-D; NCT02879305). Patients were stratified by dialysis type and were required to be on dialysis for at least 4 months prior to the first dose of JESDUVROQ. Patients on hemodialysis (HD) were randomized 1:1 to receive oral JESDUVROQ (n = 1,316) or intravenous epoetin alfa (n = 1,308) while patients on peritoneal dialysis (PD) were randomized 1:1 to receive oral JESDUVROQ (n = 171) or subcutaneous darbepoetin alfa (n = 169).

Key exclusion criteria included: ferritin ≤100 ng/ml (≤100 mcg/L), transferrin saturation ≤20% at screening; evidence of non-renal anemia; cardiovascular abnormalities (including myocardial infarction, acute coronary syndrome, stroke or transient ischemic attack within 4 weeks of screening, New York Heart Association (NYHA) Class IV heart failure, and uncontrolled hypertension); liver disease; history of malignancy within 2 years of screening; current treatment of cancer and complex kidney cyst.

Dosing in each treatment arm followed a protocol-specified adjustment algorithm to achieve and/or maintain a hemoglobin target of 10 to 11 g/dL. The starting dose of JESDUVROQ was 4 mg, 6 mg, 8 mg, or 12 mg orally once daily, based on prior ESA dose. The starting dose of either epoetin alfa (HD patients) or darbepoetin alfa (PD patients) was the same as the patient’s current dose rounded to the nearest study dose. Patients receiving other ESAs were switched to the epoetin alfa or darbepoetin alfa equivalent starting dose. The median doses at Week 52 were 6 mg per day for JESDUVROQ, 8,000 units per week for epoetin alfa, and 150 mcg every four weeks for darbepoetin alfa. Most patients (86%) were exposed to randomized treatment for greater than 6 months (median 26 months for JESDUVROQ and 26 months for rhEPO). The median number of dose adjustments from Day 1 to Week 28 was 2 (interquartile range: 1 to 3) for JESDUVROQ and 2 (interquartile range: 1 to 3) for rhEPO. The median number of dose adjustments from Week 28 to Week 52 was 1 (interquartile range: 1 to 2) for JESDUVROQ and 2 (interquartile range: 1 to 3) for rhEPO.

The mean age of the patients in this study was 57 years (range 18-95), 57% were males, 67% were Caucasian, 16% were Black, and 12% were Asian. In the US region, 39% of patients were Black. Approximately 25% of the population was Hispanic or Latino. The largest regions of enrollment were the US (29%) and Eastern Europe/South Africa (28%). Common comorbid conditions included hypertension (92%), hyperlipidemia (50%) and diabetes mellitus (42%).

Effects on Hemoglobin

The efficacy and safety of JESDUVROQ were evaluated as co-primary endpoints: the mean change in hemoglobin from baseline to the Evaluation Period (Weeks 28 to 52) and time to first adjudicated MACE (defined as all-cause mortality, non-fatal myocardial infarction, or non-fatal stroke), using a non-inferiority comparison to rhEPO (epoetin alfa and darbepoetin alfa) for both endpoints.

The lower limit of the 95% confidence interval (CI) for the overall hemoglobin treatment difference was greater than the pre-specified non-inferiority margin of -0.75 g/dL, demonstrating non-inferiority of JESDUVROQ to rhEPO with respect to the mean change in hemoglobin between baseline and over the Evaluation Period (see Table 6). Results were similar in patients receiving either hemodialysis or peritoneal dialysis.

Table 6: Change in Hemoglobin in Adults with Anemia Due to Chronic Kidney Disease Receiving Dialysis: ASCEND-D Trial (ITT Analysis)a
Assessment | JESDUVROQ; (n = 1,487) | rhEPOb; (n = 1,477)
Primary endpoint: change in Hgbc
Mean baseline Hgb, g/dL (SD) | 10.4 (1.0) | 10.4 (1.0)
Hgb change, g/dL (SE)d,e | 0.3 (0.02) | 0.1 (0.02)
Mean treatment difference (95% CI)e | 0.2 (0.1, 0.2)
Change in Hgb - hemodialysis patientsf
Number of patients | 1,316 | 1,308
Mean baseline Hgb, g/dL (SD) | 10.4 (1.0) | 10.4 (1.0)
Hgb change, g/dL (SE)d,e | 0.3 (0.02) | 0.1 (0.02)
Mean treatment difference (95% CI)e | 0.2 (0.1, 0.3)
Change in Hgb - peritoneal dialysis patientsf
Number of patients | 171 | 169
Mean baseline Hgb, g/dL (SD) | 10.3 (1.0) | 10.2 (1.0)
Hgb change, g/dL (SE)d,e | 0.4 (0.1) | 0.2 (0.1)
Mean treatment difference (95% CI)e | 0.2 (-0.04, 0.3)

CI = Confidence interval; Hgb = Hemoglobin; ITT = Intent to treat; rhEPO = Recombinant human erythropoietin; SD = Standard deviation; SE = Standard error.

a Intent to Treat (ITT) analyses included observed and imputed values on and off treatment after randomization. Eight percent of patients had no observed hemoglobin during Weeks 28 to 52.

b Hemodialysis patients received epoetin alfa and peritoneal dialysis patients received darbepoetin alfa.

c Adjusted for multiplicity.

d Mean Hgb change from baseline to Evaluation Period (EP): Weeks 28 to 52.

e Adjusted for baseline covariates.

f Not adjusted for multiplicity.

Cardiovascular Outcomes

The hazard ratio for the time to first occurrence of MACE, a composite of all-cause mortality, non‑fatal myocardial infarction, and non-fatal stroke, comparing JESDUVROQ to rhEPO was 0.93 (95% CI 0.81, 1.07) (Table 7). Non-inferiority of JESDUVROQ to rhEPO on MACE was achieved because the upper limit of the 95% CI for the MACE hazard ratio was less than the pre‑specified non-inferiority margin of 1.25.

Table 7: Major Adverse Cardiovascular Events in the ASCEND-D Trial (ITT Analysis)a
Co-primary composite endpoint | JESDUVROQ; (n = 1,487) | rhEPOb; (n = 1,477)
First occurrence of MACEc, n | 374 | 394
All‑cause mortalityd, n | 244 | 233
Non-fatal myocardial infarctiond, n | 101 | 126
Non-fatal stroked, n | 29 | 35
Hazard ratio (95% CI)e | 0.93 (0.81, 1.07)
Incidence rate per 100 PY | 11.1 | 11.9

CI = Confidence interval; ITT = Intent to treat; MACE = Major adverse cardiovascular events; PY = Person Years; rhEPO = Recombinant human erythropoietin.

a ITT analyses included events on and off treatment after randomization.

b Hemodialysis patients received epoetin alfa; peritoneal dialysis patients received darbepoetin alfa.

c Co-primary endpoint.

d Component of composite endpoint.

e Adjusted for baseline covariates.

16 HOW SUPPLIED/STORAGE AND HANDLING

How Supplied

JESDUVROQ tablets contain 1 mg, 2 mg, 4 mg, 6 mg or 8 mg of daprodustat.

Tablet; Strength | Package Configuration; and NDC Number | Tablet Description; and Markings
1 mg | 30 count bottle; (NDC 0173-0897-13) | Round, gray, biconvex, film-coated tablets debossed with “GS KF” on one side
1 mg | 100 count blister pack; (NDC 0173-0897-56) | Round, gray, biconvex, film-coated tablets debossed with “GS KF” on one side
2 mg | 30 count bottle; (NDC 0173-0903-13) | Round, yellow, biconvex, film-coated tablets debossed with “GS V7” on one side
2 mg | 100 count blister pack; (NDC 0173-0903-56) | Round, yellow, biconvex, film-coated tablets debossed with “GS V7” on one side
4 mg | 30 count bottle; (NDC 0173-0906-13) | Round, white, biconvex, film-coated tablets debossed with “GS 13” on one side
4 mg | 100 count blister pack; (NDC 0173-0906-56) | Round, white, biconvex, film-coated tablets debossed with “GS 13” on one side
6 mg | 30 count bottle; (NDC 0173-0911-13) | Round, pink, biconvex, film-coated tablets debossed with “GS IM” on one side
6 mg | 100 count blister pack; (NDC 0173-0911-56) | Round, pink, biconvex, film-coated tablets debossed with “GS IM” on one side
8 mg | 30 count bottle; (NDC 0173-0914-13) | Round, orange, biconvex, film-coated tablets debossed with “GS 5E” on one side
8 mg | 100 count blister pack; (NDC 0173-0914-56) | Round, orange, biconvex, film-coated tablets debossed with “GS 5E” on one side

Storage and Handling

Store at 20°C to 25°C (68°F to 77°F); excursions permitted between 15°C and 30°C (59°F to 86°F). [See USP Controlled Room Temperature].

17 PATIENT COUNSELING INFORMATION

Advise the patient to read the FDA-approved patient labeling (Medication Guide).

Inform patients:

- Of the increased risks of death, myocardial infarction, stroke, venous thromboembolism, and thrombosis of vascular access [see Warnings and Precautions (5.1)].
- Of the risk of hospitalization due to heart failure, the symptoms and signs of heart failure and to promptly report these symptoms to their healthcare provider [see Warnings and Precautions (5.2)].
- Of the risk of hypertension, to undergo regular blood pressure monitoring and to adhere to the prescribed anti-hypertensive regimen [see Warnings and Precautions (5.3)].
- Of the risk of gastric erosions and gastrointestinal bleeding, the associated symptoms and signs and to report these symptoms to their healthcare provider [see Warnings and Precautions (5.4)].
- Of the need to have regular laboratory tests for hemoglobin [see Dosage and Administration (2.1, 2.4)].
- Of the need to inform their healthcare provider if they are taking strong CYP2C8 inhibitors, including gemfibrozil or moderate CYP2C8 inhibitors [see Contraindications (4), Drug Interactions (7.1)].
- Pregnancy
JESDUVROQ may cause fetal harm. Advise females to inform their healthcare provider of a known or suspected pregnancy [see Use in Specific Populations (8.1)].
- Lactation
Advise females not to breastfeed during treatment with JESDUVROQ and for one week after the final dose [see Use in Specific Populations (8.2)].

Trademarks are owned by or licensed to the GSK group of companies.

Manufactured by

GlaxoSmithKline

Durham, NC 27701

©2023 GSK group of companies or its licensor.

JDV:3PI

MEDICATION GUIDE

PHARMACIST - DETACH HERE AND GIVE INSTRUCTIONS TO PATIENT

- - - - - - - - - - - - - - - - - - - - - - - - - - - - - - - - - - - - - - - - - - - - - - - - - - - - - - - - - - - - - - - - - - -

MEDICATION GUIDE

JESDUVROQ (jez–DOOV–rok)

(daprodustat)

tablets

What is the most important information I should know about JESDUVROQ?

JESDUVROQ may cause serious side effects, including:

- Increased risk of death, heart attack, stroke, and blood clots. These risks may happen if you are treated with JESDUVROQ to increase red blood cells (RBCs) to near the same level found in healthy people. These risks may be increased if you have heart or blood vessel problems, or problems with blood flow to your brain (cerebrovascular disease). Blood clots can form in the blood vessels (veins), including in your legs (deep vein thrombosis or DVT), lungs (pulmonary embolism or PE), and in your dialysis access (vascular access thrombosis or VAT).
Get medical help right away if you get any of the following symptoms:

○chest pain

○sudden trouble seeing

○trouble breathing or shortness of breath

○sudden trouble walking, dizziness, loss of balance or coordination

○pain in your leg or arm, with or without swelling

○lightheadedness or fainting

○unusual coolness or warmth in arm or leg

○dialysis access stops working

○sudden confusion, trouble speaking, or trouble understanding others’ speech

○do not feel a vibration (“thrill”) over the dialysis access area

○sudden numbness or weakness in your face, arm, or leg, especially on one side of your body

See “What are the possible side effects of JESDUVROQ?” for more information about side effects.

If you decide to take JESDUVROQ, your healthcare provider should prescribe the lowest dose of JESDUVROQ that is necessary to reduce your chance of needing red blood cell transfusions.

What is JESDUVROQ?

JESDUVROQ is a prescription medicine used to treat anemia that is caused by chronic kidney disease (CKD) in adults who have been on dialysis for at least 4 months. People with anemia have a lower-than-normal number of RBCs. JESDUVROQ works by increasing a protein called erythropoietin to help your body make more RBCs. JESDUVROQ is used to reduce or avoid the need for RBC transfusions.

If your hemoglobin level stays too high or if your hemoglobin goes up too quickly, this may lead to serious health problems which may result in death. These serious health problems may happen if you take JESDUVROQ, even if you do not have an increase in your hemoglobin levels.

JESDUVROQ has not been proven to improve quality of life, tiredness (fatigue), or well-being.

JESDUVROQ should not be used:

- in place of emergency treatment for anemia (red blood cell transfusions).
- for the treatment of anemia that is caused by CKD in people who are not on dialysis. It is not known if JESDUVROQ is safe and effective in children.

Do not take JESDUVROQ if you:

- take certain medicines called strong CYP2C8 inhibitors such as gemfibrozil. Ask your healthcare provider if you are not sure.
- have high blood pressure that is not controlled (uncontrolled hypertension)

Before taking JESDUVROQ, tell your healthcare provider about all of your medical conditions, including if you:

- have heart disease
- have had a stroke
- have a history of heart failure
- have high blood pressure
- have a history of damage to the lining of the stomach, the tube that connects the mouth and stomach (esophagus), or intestines
- have a history of stomach ulcers (peptic ulcer disease)
- smoke tobacco or drink alcohol
- have cancer
- have liver problems
- are pregnant or plan to become pregnant. JESDUVROQ may cause harm to your unborn baby. Tell your healthcare provider right away if you become pregnant or think you might be pregnant during treatment with JESDUVROQ.
- are breastfeeding or plan to breastfeed. It is not known if JESDUVROQ passes into your breast milk. Do not breastfeed during treatment with JESDUVROQ and for 1 week after your final dose.

Tell your healthcare provider about all the medicines you take, including prescription and over-the-counter medicines, vitamins, and herbal supplements. Taking JESDUVROQ with certain other medicines may affect the way JESDUVROQ works.

How should I take JESDUVROQ?

- Take JESDUVROQ exactly as your healthcare provider tells you to take it.
- Do not change your dose or stop JESDUVROQ without talking to your healthcare provider.
- Take your prescribed dose of JESDUVROQ 1 time a day.
- Swallow JESDUVROQ tablets whole. Do not cut, crush, or chew the tablet.
- JESDUVROQ can be taken with or without food.
- JESDUVROQ can be taken at the same time as iron supplements or medicines that control the amount of phosphorus in your blood (phosphate binders), if necessary.
- If you miss a dose of JESDUVROQ, take it as soon as you remember. If it is the same day as your next dose, skip the missed dose and take your next dose at your usual time. Do not take 2 doses at the same time to make up for the missed dose.
- If you take more than your prescribed dose of JESDUVROQ, contact your healthcare provider or go to the nearest hospital emergency room right away.
- Your healthcare provider will do certain blood tests before you start JESDUVROQ and during treatment as needed. Your healthcare provider may change your dose of JESDUVROQ based on the results of your blood tests.

What are the possible side effects of JESDUVROQ?

JESDUVROQ may cause serious side effects, including:

- See “What is the most important information I should know about JESDUVROQ?”
- Risk of hospitalization for heart failure. People who have a history of heart failure have an increased risk of hospitalization for heart failure with JESDUVROQ. Tell your healthcare provider right away if you get worsening signs and symptoms of heart failure, including:

○shortness of breath or trouble breathing

○sudden weight gain

○swelling of your feet, ankles or legs

○feeling tired or weak

- High blood pressure. High blood pressure is common with JESDUVROQ. Your blood pressure may go up or worsen, and may be difficult to treat during treatment with JESDUVROQ. Your healthcare provider should check your blood pressure regularly during treatment with JESDUVROQ. If your blood pressure increases, your healthcare provider may prescribe a new medicine or may change the dose of your current blood pressure medicine.
- Damage to the lining of the stomach, the tube that connects the mouth and stomach (esophagus), and intestines (gastrointestinal erosion). Your risk of gastrointestinal erosion may increase if you have a history of gastrointestinal erosion, stomach ulcers (peptic ulcer disease), use certain medicines that increase the risk of gastrointestinal erosion, or currently smoke tobacco or drink alcohol. Some people who have bleeding in the stomach and intestines may need to receive transfusions. Tell your healthcare provider if you have any of these symptoms:

○stomach-area (abdominal) discomfort or pain

○black, tarry stools

○nausea or vomiting

○trouble swallowing

○blood in your vomit or stool

○pain in your throat or chest

- Cancer. Cancers have happened in people treated with JESDUVROQ. Talk to your healthcare provider if you have any concerns about cancer.

The most common side effects of JESDUVROQ include:

- high blood pressure. See “High blood pressure” above.
- heart attack, stroke, and blood clots in the dialysis access, legs, or lungs. See “What is the most important information I should know about JESDUVROQ?” above.
- stomach area (abdominal) pain.

These are not all the possible side effects of JESDUVROQ.

Call your doctor for medical advice about side effects. You may report side effects to FDA at 1-800-FDA-1088.

How should I store JESDUVROQ?

- Store JESDUVROQ at room temperature between 68°F to 77°F (20°C to 25°C).

Keep JESDUVROQ and all medicines out of the reach of children.

General information about the safe and effective use of JESDUVROQ.

Medicines are sometimes prescribed for purposes other than those listed in a Medication Guide. Do not use JESDUVROQ for a condition for which it was not prescribed. Do not give JESDUVROQ to other people, even if they have the same symptoms that you have. It may harm them.

You can ask your pharmacist or healthcare provider for information about JESDUVROQ that is written for health professionals.

What are the ingredients in JESDUVROQ?

Active Ingredient: daprodustat.

Inactive Ingredients: colloidal silicon dioxide, croscarmellose sodium, hypromellose, magnesium stearate, mannitol, and microcrystalline cellulose.

Tablet film-coating: hypromellose, iron oxide black (1 mg, 2 mg, and 6 mg tablets), iron oxide red and iron oxide yellow (1 mg, 2 mg, 6 mg, and 8 mg tablets), polyethylene glycol, and titanium dioxide.

Trademarks are owned by or licensed to the GSK group of companies.

Manufactured by

GlaxoSmithKline

Durham, NC 27701

©2023 GSK group of companies or its licensor.

JDV:1MG

For more information, go to www.JESDUVROQ.com or call GlaxoSmithKline (GSK) at 1-888-825-5249.

This Medication Guide has been approved by the U.S. Food and Drug Administration Issued: February 2023

PACKAGE LABEL

PRINCIPAL DISPLAY PANEL

NDC 0173-0897-13

Jesduvroq

(daprodustat) tablets

1 mg

Rx only

GSK

Dispense the accompanying Medication Guide to each patient

30 tablets

Each tablet contains 1 mg of daprodustat.

Swallow tablets whole. Do not cut, crush or chew the tablet.

Store at 20°C to 25°C (68°F to 77°F); exclusions permitted between 15°C and 30°C (59°F to 86°F). [See USP Controlled Room Temperatures].

Do not accept if safety seal under cap is broken or missing.

Recommended Dosage:

See Prescribing Information.

Trademarks are owned by or licensed to the GSK group of companies.

Mfd. By: GlaxoSmithKline

Durham, NC 27701

Product of Singapore

©2023 GSK or licensor.

Rev. 3/23

A087261 (62000000087261)

PACKAGE LABEL

PRINCIPAL DISPLAY PANEL

NDC 0173-0903-13

Jesduvroq

(daprodustat) tablets

2 mg

Rx only

GSK

Dispense the accompanying Medication Guide to each patient

30 tablets

Each tablet contains 2 mg of daprodustat.

Swallow tablets whole. Do not cut, crush or chew the tablet.

Store at 20°C to 25°C (68°F to 77°F); exclusions permitted between 15°C and 30°C (59°F to 86°F). [See USP Controlled Room Temperatures].

Do not accept if safety seal under cap is broken or missing.

Recommended Dosage:

See Prescribing Information.

Trademarks are owned by or licensed to the GSK group of companies.

Mfd. By: GlaxoSmithKline

Durham, NC 27701

Product of Singapore

©2023 GSK or licensor.

Rev. 3/23

A087262 (62000000087262)

PACKAGE LABEL

PRINCIPAL DISPLAY PANEL

NDC 0173-0906-13

Jesduvroq

(daprodustat) tablets

4 mg

Rx only

GSK

Dispense the accompanying Medication Guide to each patient

30 tablets

Each tablet contains 4 mg of daprodustat.

Swallow tablets whole. Do not cut, crush or chew the tablet.

Store at 20°C to 25°C (68°F to 77°F); exclusions permitted between 15°C and 30°C (59°F to 86°F). [See USP Controlled Room Temperatures].

Do not accept if safety seal under cap is broken or missing.

Recommended Dosage:

See Prescribing Information.

Trademarks are owned by or licensed to the GSK group of companies.

Mfd. By: GlaxoSmithKline

Durham, NC 27701

Product of Singapore

©2023 GSK or licensor.

Rev. 3/23

A087263 (62000000087263)

PACKAGE LABEL

PRINCIPAL DISPLAY PANEL

NDC 0173-0911-13

Jesduvroq

(daprodustat) tablets

6 mg

Rx only

GSK

Dispense the accompanying Medication Guide to each patient

30 tablets

Each tablet contains 6 mg of daprodustat.

Swallow tablets whole. Do not cut, crush or chew the tablet.

Store at 20°C to 25°C (68°F to 77°F); exclusions permitted between 15°C and 30°C (59°F to 86°F). [See USP Controlled Room Temperatures].

Do not accept if safety seal under cap is broken or missing.

Recommended Dosage:

See Prescribing Information.

Trademarks are owned by or licensed to the GSK group of companies.

Mfd. By: GlaxoSmithKline

Durham, NC 27701

Product of Singapore

©2023 GSK or licensor.

Rev. 3/23

A087264 (62000000087264)

PACKAGE LABEL

PRINCIPAL DISPLAY PANEL

NDC 0173-0914-13

Jesduvroq

(daprodustat) tablets

8 mg

Rx only

GSK

Dispense the accompanying Medication Guide to each patient

30 tablets

Each tablet contains 8 mg of daprodustat.

Swallow tablets whole. Do not cut, crush or chew the tablet.

Store at 20°C to 25°C (68°F to 77°F); exclusions permitted between 15°C and 30°C (59°F to 86°F). [See USP Controlled Room Temperatures].

Do not accept if safety seal under cap is broken or missing.

Recommended Dosage:

See Prescribing Information.

Trademarks are owned by or licensed to the GSK group of companies.

Mfd. By: GlaxoSmithKline

Durham, NC 27701

Product of Singapore

©2023 GSK or licensor.

Rev. 3/23

A087265 (62000000087265)